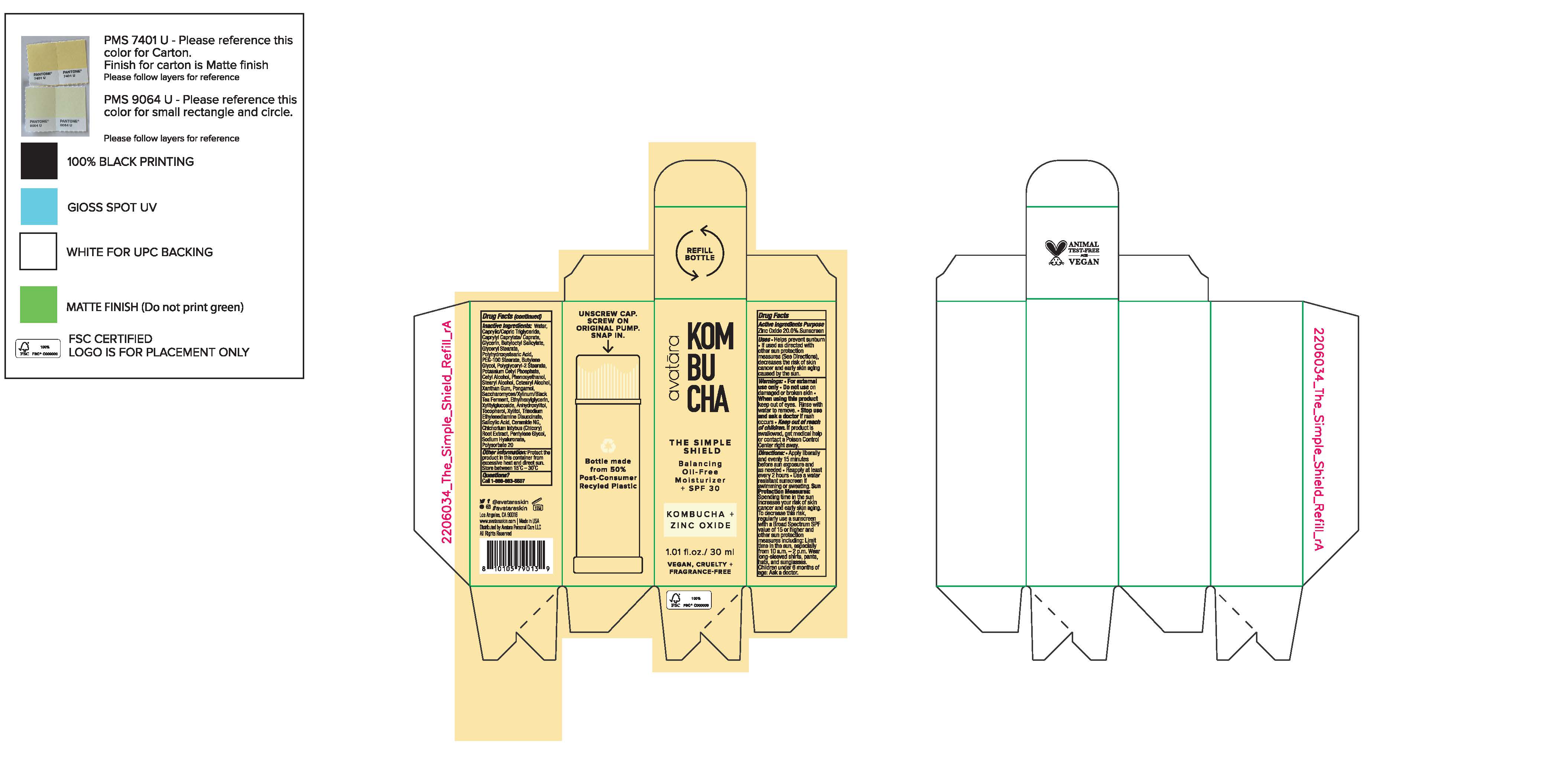 DRUG LABEL: avatara Kom Bu Cha The Simple Shield Balancing Oil-Free Moisturizer SPF 30
NDC: 83126-101 | Form: LOTION
Manufacturer: Avatara Personal Care LLC
Category: otc | Type: HUMAN OTC DRUG LABEL
Date: 20260218

ACTIVE INGREDIENTS: ZINC OXIDE 20 g/100 g
INACTIVE INGREDIENTS: WATER; CAPRYLYL CAPRYLATE/CAPRATE; GLYCINE; BUTYLOCTYL SALICYLATE; GLYCERYL STEARATE SE; POLYHYDROXYSTEARIC ACID (2300 MW); PEG-100 STEARATE; BUTYLENE GLYCOL; POLYGLYCERYL-2 STEARATE; POTASSIUM CETYL PHOSPHATE; CETYL ALCOHOL; XANTHAN GUM; PONGAMOL; ETHYLHEXYLGLYCERIN; XYLITYLGLUCOSIDE; ANHYDROXYLITOL; ALPHA-TOCOPHEROL; XYLITOL; TRISODIUM ETHYLENEDIAMINE DISUCCINATE; SALICYLIC ACID; CERAMIDE NG; CHICORY ROOT; PENTYLENE GLYCOL; POLYSORBATE 20

DRUG FACTS

Active Ingredients

Zinc Oxide 20%

Uses

• helps prevent sunburn • if used as directed with other
sun protection measures (see Directions), decreases the
risk of skin cancer and early skin aging caused by the sun

Warnings

For external use only
Do not use on damaged or broken skin
When using this product keep out of eyes. Rinse with water to remove.
Stop use and ask a docor if rash occurs
Keep out of reach of children. If swalled, get medical help or contact a Poison Control Center right away.

Directions

• apply generously 15 minutes before sun exposure
• reapply at least every 2 hours
• use a water-resistant sunscreen if swimming or sweating
• Sun Protection Measures. Spending time in the sun
increases your risk of skin cancer and early skin aging. To decrease
this risk, regularly use a sunscreen with a Broad Spectrum SPF
value of 15 or higher and other sun protection measures including:
• limit time in the sun, especially from 10 a.m. - 2 p.m.
• wear long-sleeved shirts, pants, hats, and sunglasses
• children under 6 months of age: Ask a doctor

Inactive ingredients

Water, Caprylic/Capric Triglyceride, Caprylyl Caprylate/Caprate, Glycerin, Butyloctyl Salicylate, Glyceryl Stearate, Polyhydrostearic Acid, PEG-100 Stearate, Butylene Glycol, Polyglyceryl-2 Stearate, Potassium Cetyl Phosphate, Cetyl Alcohol, Cetearyl Alcohol, Xanthan Gum, Pongamol, Saccharomyces/Xylinum/Black Tea Ferment, Ethylhexylglycerin, Xylitylglucoside, Anhydroxylitol, Tocopherol, Xylitol, Trisodium Ethylenediamine Disuccinate, Salicylic Acid, Ceramide NG, Chichorium Intybus (Chicory) Root Extract, Pentylene Glycol, Sodium Hyaluronate, Polysorbate 20

Other Information

• protect the product in this container from excessive
heat and direct sun

Questions?

Call 1-888-883-5507

Keep out of reach of children.

Purpose

Sunscreen